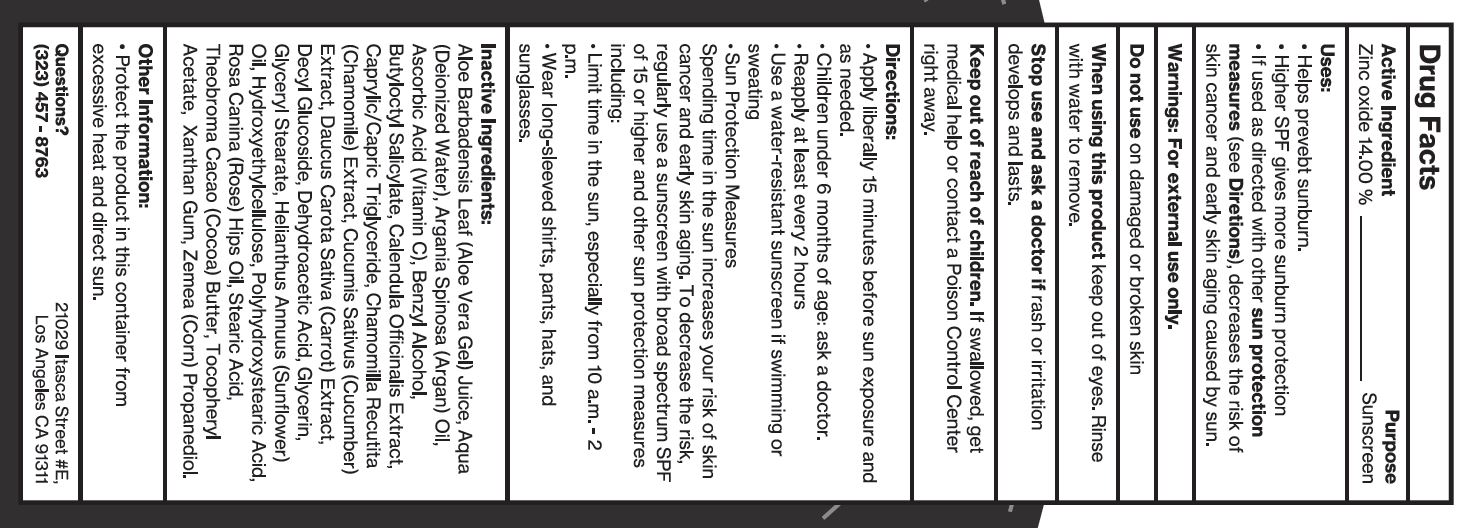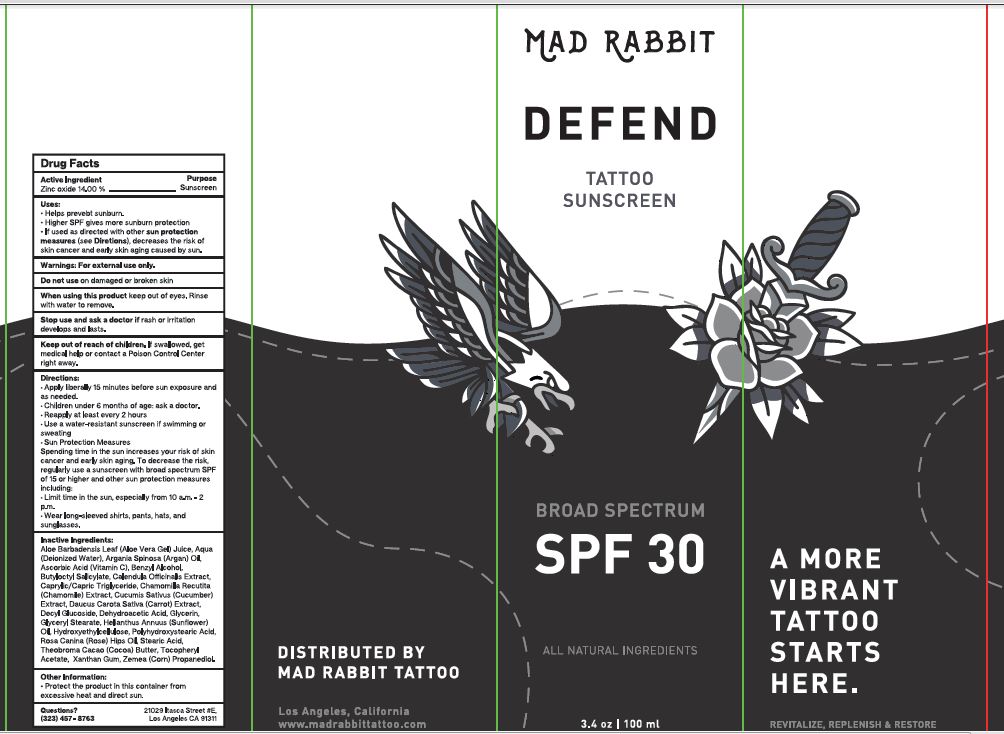 DRUG LABEL: Defend tattoo sunscreen SPF 30
NDC: 80396-079 | Form: CREAM
Manufacturer: Rabbit Mad Tattoo LLC
Category: otc | Type: HUMAN OTC DRUG LABEL
Date: 20241220

ACTIVE INGREDIENTS: ZINC OXIDE 140 mg/1 mL
INACTIVE INGREDIENTS: ALOE VERA LEAF; WATER; ARGAN OIL; ASCORBIC ACID; BENZYL ALCOHOL; BUTYLOCTYL SALICYLATE; CALENDULA OFFICINALIS FLOWER; MEDIUM-CHAIN TRIGLYCERIDES; CHAMOMILE; CUCUMBER; CARROT; DECYL GLUCOSIDE; DEHYDROACETIC ACID; GLYCERIN; GLYCERYL MONOSTEARATE; HELIANTHUS ANNUUS FLOWERING TOP; HYDROXYETHYL CELLULOSE, UNSPECIFIED; POLYHYDROXYSTEARIC ACID (2300 MW); ROSE OIL; STEARIC ACID; COCOA; .ALPHA.-TOCOPHEROL ACETATE; XANTHAN GUM; CORN

Defend tattoo sunscreen spf 30

Active Ingredient

Zinc oxide 14.00 %

Purpose

Sunscreen

Uses:

- Helps prevebt sunburn.
- Higher SPF gives more sunburn protection
- If used as directed with other sun protection measures (see Diretions), decreases the risk of skin cancer and early skin aging caused by sun.

Warnings:

For external use only.

Do not use

on damaged or broken skin

When using this product

keep out of eyes. Rinse with water to remove.

Stop use and ask a doctor

if rash or irritation develops and lasts.

Keep out of reach of children.

If swallowed, get medical help or contact a Poison Control Center right away.

Directions:

• Apply liberally 15 minutes before sun exposure and as needed. • Children under 6 months of age: ask a doctor. • Reapply at least every 2 hours • Use a water-resistant sunscreen if swimming or sweating • Sun Protection Measures Spending time in the sun increases your risk of skin cancer and early skin aging. To decrease the risk, regularly use a sunscreen with broad spectrum SPF of 15 or higher and other sun protection measures including: • Limit time in the sun, especially from 10 a.m. - 2 p.m. • Wear long-sleeved shirts, pants, hats, and sunglasses.

Inactive Ingredients:

Aloe Barbadensis Leaf (Aloe Vera Gel) Juice, Aqua (Deionized Water), Argania Spinosa (Argan) Oil, Ascorbic Acid (Vitamin C), Benzyl Alcohol, Butyloctyl Salicylate, Calendula Officinalis Extract, Caprylic/Capric Triglyceride, Chamomilla Recutita (Chamomile) Extract, Cucumis Sativus(Cucumber) Extract, Daucus Carota Sativa (Carrot) Extract, Decyl Glucoside, Dehydroacetic Acid, Glycerin, Glyceryl Stearate, Helianthus Annuus (Sunflower) Oil, Hydroxyethylcellulose, Polyhydroxystearic Acid, Rosa Canina (Rose) Hips Oil, Stearic Acid, Theobroma Cacao (Cocoa) Butter, Tocopheryl Acetate (Vitamin E), Xanthan Gum, Zemea (Corn) Propanediol.

Other Information:

- Protect the product in this container from excessive heat and direct sun.

Questions?

(323) 457 - 8763